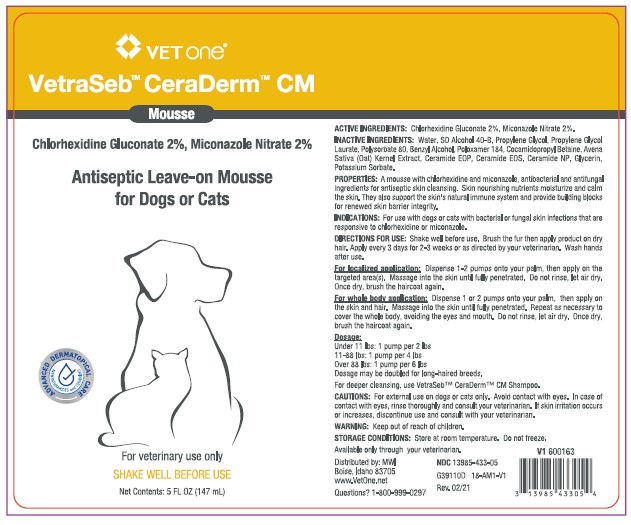 DRUG LABEL: VetraSeb CeraDerm
NDC: 13985-433 | Form: LIQUID
Manufacturer: MWI/VETONE
Category: animal | Type: OTC ANIMAL DRUG LABEL
Date: 20210519

ACTIVE INGREDIENTS: CHLORHEXIDINE GLUCONATE 20 mg/1 mL; MICONAZOLE NITRATE 20 mg/1 mL
INACTIVE INGREDIENTS: WATER; ALCOHOL; PROPYLENE GLYCOL; PROPYLENE GLYCOL LAURATES; POLYSORBATE 80; BENZYL ALCOHOL; POLOXAMER 184; COCAMIDOPROPYL BETAINE; AVENANTHRAMIDES; CERAMIDE 1; CERAMIDE EOS; CERAMIDE NP; GLYCERIN; POTASSIUM SORBATE

DESCRIPTION

VetraSeb™ CeraDerm™ CM Mousse

Antiseptic Leave-on Mousse for Dogs or Cats

ACTIVE INGREDIENTS: Chlorhexidine Gluconate 2%, Miconazole Nitrate 2%.

INACTIVE INGREDIENTS: Water, SD Alcohol 40-B, Propylene Glycol, Propylene Glycol Laurate, Polysorbate 80, Benzyl Alcohol, Poloxamer 184, Cocamidopropyl Betaine, Avena Sativa (Oat) Kernel Extract, Ceramide EOP, Ceramide EOS, Ceramide NP, Glycerin, Potasssium Sorbate.

PROPERTIES: A mousse with chlorhexidine and miconazole, antibacterial and antifungal ingredients for antiseptic skin cleansing. Skin nourishing nutrients moisturize and calm the skin. They also support the skin’s natural immune system and provide building blocks for renewed skin barrier integrity.

INDICATIONS AND USAGE

INDICATIONS: For use on dogs or cats with bacterial or fungal skin infections that are responsive to chlorhexidine or miconazole.

DIRECTIONS FOR USE: Shake well before use.Brush the fur and then apply on dry hair. Apply every 3 days for 2-3 weeks or as directed by your veterinarian. Wash hands after use.

For localized application: Dispense 1 or 2 pumps onto your palm and then apply on the targeted area(s). Massage into the skin until fully penetrated. Do not rinse, let air dry. Once dry, brush the haircoat again.

For whole body application: Dispense 1 or 2 pumps onto your palm and then apply on the skin and hair. Massage into the skin until fully penetrated. Repeat as necessary to cover the whole body, avoiding the eyes and mouth. Do not rinse, let air dry. Once dry, brush the haircoat again.

Dosage:
Under 11 lbs: 1 pump per 2 lbs
11-88 lbs: 1 pump per 4 lbs
Over 88 lbs: 1 pump per 6 lbs
Dosage may be doubled for long-haired dogs.

For deeper cleansing, use VetraSeb™ CeraDerm™ CM Shampoo.

WARNINGS AND PRECAUTIONS

CAUTIONS: For external use on dogs or cats only. Avoid contact with eyes. In case of contact with eyes, rinse thoroughly and consult your veterinarian. If skin irritation occurs or increases, discontinue use and consult with your veterinarian.

WARNINGS: Keep out of reach of children.

STORAGE AND HANDLING

STORAGE CONDITIONS: Store at room temperature. Do not freeze.

Available only through your veterinarian

Distributed by: MWI

Boise, Idaho 83705

www.VetOne.net

QUESTIONS? 1-800-999-0297

PRINCIPAL DISPLAY PANEL - 5 OUNCE (148 mL) Bottle

VETone©

VetraSeb™ CeraDerm™ CM

Mousse

Chlorhexidine Gluconate 2%, Miconazole 2%

Antiseptic Leave-on Mousse for Dogs or Cats

For veterinary use only

SHAKE WELL BEFORE USE

Net contents: 5 fl oz (148 mL)